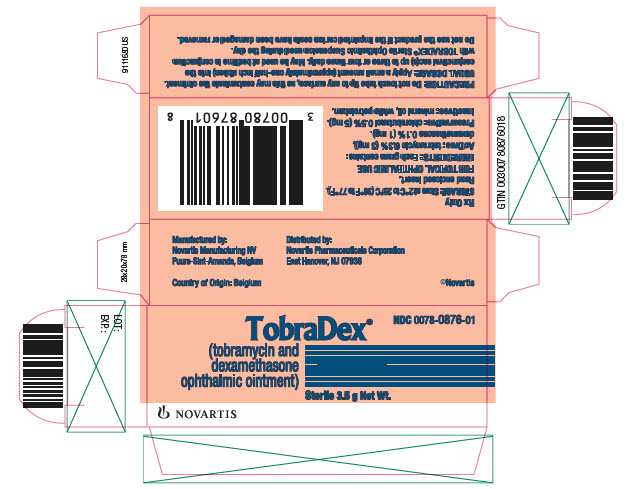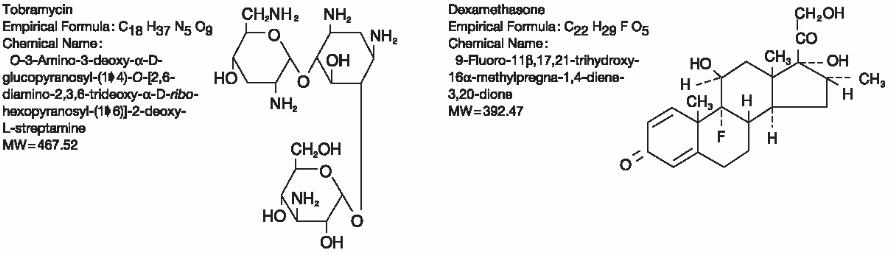 DRUG LABEL: TobraDex
NDC: 0078-0876 | Form: OINTMENT
Manufacturer: Novartis Pharmaceuticals Corporation
Category: prescription | Type: HUMAN PRESCRIPTION DRUG LABEL
Date: 20250926

ACTIVE INGREDIENTS: TOBRAMYCIN 3 mg/1 g; DEXAMETHASONE 1 mg/1 g
INACTIVE INGREDIENTS: CHLOROBUTANOL; MINERAL OIL; PETROLATUM

TobraDex® (tobramycin and dexamethasone ophthalmic ointment) Sterile

DESCRIPTION

DESCRIPTION: TOBRADEX® (tobramycin and dexamethasone ophthalmic ointment) is a sterile, multiple dose antibiotic and steroid combination for topical ophthalmic use. The chemical structures for tobramycin and dexamethasone are presented below:

Each gram of TOBRADEX® (tobramycin and dexamethasone ophthalmic ointment) contains: Actives: tobramycin 0.3% (3 mg) and dexamethasone 0.1% (1 mg). Preservative: chlorobutanol 0.5%. Inactives: mineral oil and white petrolatum.

CLINICAL PHARMACOLOGY

CLINICAL PHARMACOLOGY: Corticoids suppress the inflammatory response to a variety of agents and they probably delay or slow healing. Since corticoids may inhibit the body's defense mechanism against infection, a concomitant antimicrobial drug may be used when this inhibition is considered to be clinically significant. Dexamethasone is a potent corticoid.

The antibiotic component in the combination (tobramycin) is included to provide action against susceptible organisms. In vitro studies have demonstrated that tobramycin is active against susceptible strains of the following microorganisms:

Staphylococci, including S. aureus and S. epidermidis (coagulase-positive and coagulase-negative), including penicillin-resistant strains.

Streptococci, including some of the Group A-beta-hemolytic species, some nonhemolytic species, and some Streptococcus pneumoniae.

Pseudomonas aeruginosa, Escherichia coli, Klebsiella pneumoniae, Enterobacter aerogenes, Proteus mirabilis, Morganella morganii, most Proteus vulgaris strains, Haemophilus influenzae and H. aegyptius, Moraxella lacunata, Acinetobacter calcoaceticus and some Neisseria species.

No data are available on the extent of systemic absorption from TOBRADEX® (tobramycin and dexamethasone ophthalmic ointment); however, it is known that some systemic absorption can occur with ocularly applied drugs.

INDICATIONS AND USAGE: TOBRADEX (tobramycin and dexamethasone ophthalmic ointment) is indicated for steroid-responsive inflammatory ocular conditions for which a corticosteroid is indicated and where superficial bacterial ocular infection or a risk of bacterial ocular infection exists.

Ocular steroids are indicated in inflammatory conditions of the palpebral and bulbar conjunctiva, cornea and anterior segment of the globe where the inherent risk of steroid use in certain infective conjunctivitides is accepted to obtain a diminution in edema and inflammation. They are also indicated in chronic anterior uveitis and corneal injury from chemical, radiation or thermal burns, or penetration of foreign bodies.

The use of a combination drug with an anti-infective component is indicated where the risk of superficial ocular infection is high or where there is an expectation that potentially dangerous numbers of bacteria will be present in the eye.

The particular anti-infective drug in this product is active against the following common bacterial eye pathogens:

Staphylococci, including S. aureus and S. epidermidis (coagulase-positive and coagulase-negative), including penicillin-resistant strains.

Streptococci, including some of the Group A-beta-hemolytic species, some nonhemolytic species, and some Streptococcus pneumoniae.

Pseudomonas aeruginosa, Escherichia coli, Klebsiella pneumoniae, Enterobacter aerogenes, Proteus mirabilis, Morganella morganii, most Proteus vulgaris strains, Haemophilus influenzae and H. aegyptius, Moraxella lacunata, Acinetobacter calcoaceticus and some Neisseria species.

CONTRAINDICATIONS

CONTRAINDICATIONS: Epithelial herpes simplex keratitis (dendritic keratitis), vaccinia, varicella, and many other viral diseases of the cornea and conjunctiva. Mycobacterial infection of the eye. Fungal diseases of ocular structures. Hypersensitivity to a component of the medication.

WARNINGS:

FOR TOPICAL OPHTHALMIC USE. NOT FOR INJECTION INTO THE EYE. Sensitivity to topically applied aminoglycosides may occur in some patients. Severity of hypersensitivity reactions may vary from local effects to generalized reactions such erythema, itching, urticaria, skin rash, anaphylaxis, anaphylactoid reactions, or bullous reactions. If a sensitivity reaction does occur, discontinue use.

Prolonged use of steroids may result in glaucoma, with damage to the optic nerve, defects in visual acuity and fields of vision, and posterior subcapsular cataract formation. Intraocular pressure (IOP) should be routinely monitored even though it may be difficult in pediatric patients and uncooperative patients. Prolonged use may suppress the host response and thus increase the hazard of secondary ocular infections. In acute purulent conditions and parasitic infections of the eye, steroids may mask infection or enhance existing infection. In those diseases causing thinning of the cornea or sclera, perforations have been known to occur with the use of topical steroids.

PRECAUTIONS:

GENERAL PRECAUTIONS

General: The possibility of fungal infections of the cornea should be considered after long-term steroid dosing. As with other antibiotic preparations, prolonged use may result in overgrowth of nonsusceptible organisms, including fungi. If superinfection occurs, appropriate therapy should be initiated. When multiple prescriptions are required, or whenever clinical judgement dictates, the patient should be examined with the aid of magnification, such as slit lamp biomicroscopy and, where appropriate, fluorescein staining.

Cross-sensitivity to other aminoglycoside antibiotics may occur; if hypersensitivity develops with this product, discontinue use and institute appropriate therapy.

Ophthalmic ointment may retard corneal wound healing.

Patients should be advised not to wear contact lenses if they have signs and symptoms of bacterial ocular infection.

PATIENT COUNSELING INFORMATION

Information for Patients: Do not touch tube tip to any surface, as this may contaminate the contents. Contact lenses should not be worn during the use of this product.

Do not use the product if the imprinted carton seals have been damaged, or removed.

CARCINOGENESIS AND MUTAGENESIS AND IMPAIRMENT OF FERTILITY

Carcinogenesis, Mutagenesis, Impairment of Fertility: No studies have been conducted to evaluate the carcinogenic or mutagenic potential. No impairment of fertility was noted in studies of subcutaneous tobramycin in rats at doses of 50 and 100 mg/kg/day.

PREGNANCY

Pregnancy: Corticosteroids have been found to be teratogenic in animal studies. Ocular administration of 0.1% dexamethasone resulted in 15.6% and 32.3% incidence of fetal anomalies in two groups of pregnant rabbits. Fetal growth retardation and increased mortality rates have been observed in rats with chronic dexamethasone therapy. Reproduction studies have been performed in rats and rabbits with tobramycin at doses up to 100 mg/kg/day parenterally and have revealed no evidence of impaired fertility or harm to the fetus.

There are no adequate and well-controlled studies in pregnant women. However, prolonged or repeated corticoid use during pregnancy has been associated with an increased risk of intra-uterine growth retardation. TOBRADEX® (tobramycin and dexamethasone ophthalmic ointment) should be used during pregnancy only if the potential benefit justifies the potential risk to the fetus. Infants born of mothers who have received substantial doses of corticosteroids during pregnancy should be observed carefully for signs of hypoadrenalism.

NURSING MOTHERS

Nursing Mothers: Systemically administered corticosteroids appear in human milk and could suppress growth, interfere with endogenous corticosteroid production, or cause other untoward effects. It is not known whether topical administration of corticosteroids could result in sufficient systemic absorption to produce detectable quantities in human milk. Because many drugs are excreted in human milk, caution should be exercised when TOBRADEX® (tobramycin and dexamethasone ophthalmic ointment) is administered to a nursing woman.

PEDIATRIC USE

Pediatric Use: Safety and effectiveness in pediatric patients below the age of 2 years have not been established.

GERIATRIC USE

Geriatric Use: No overall clinical differences in safety or effectiveness have been observed between the elderly and other adult patients.

ADVERSE REACTIONS

ADVERSE REACTIONS: Adverse reactions have occurred with steroid/anti-infective combination drugs which can be attributed to the steroid component, the anti-infective component, or the combination. Exact incidence figures are not available.

The most frequent adverse reactions to topical ocular tobramycin [TOBREX® (tobramycin ophthalmic ointment) 0.3%] are hypersensitivity and localized ocular toxicity, including lid itching and swelling, and conjunctival erythema. These reactions occur in less than 4% of patients.

The reactions due to the steroid component are: elevation of intraocular pressure with possible development of glaucoma, and infrequent optic nerve damage; posterior subcapsular cataract formation; and delayed wound healing.

Secondary Infection. The development of secondary infection has occurred after use of combinations containing steroids and antimicrobials. Fungal infections of the cornea are particularly prone to develop coincidentally with long-term applications of steroids. The possibility of fungal invasion must be considered in any persistent corneal ulceration where steroid treatment has been used. Secondary bacterial ocular infection following suppression of host responses also occurs.

POSTMARKETING EXPERIENCE

Postmarketing Experience: Additional adverse reactions identified from postmarketing use include, anaphylactic reaction, erythema multiforme.

The following additional adverse reactions have been reported with the individual components listed below:

Dexamethasone: Cushing’s syndrome and adrenal suppression may occur after use of dexamethasone in excess of the listed dosing instructions in predisposed patients, including children and patients treated with CYP3A4 inhibitors.

Aminoglycosides: Neurotoxicity, ototoxicity, and nephrotoxicity have occurred in patients receiving systemic aminoglycoside therapy. Aminoglycosides may aggravate muscle weakness in patients with known or suspected neuromuscular disorders, such as myasthenia gravis or Parkinson’s disease, because of their potential effect on neuromuscular function.

DOSAGE AND ADMINISTRATION: Apply a small amount (approximately ½ inch ribbon) into the conjunctival sac(s) up to three or four times daily.

How to apply TOBRADEX® (tobramycin and dexamethasone ophthalmic ointment):

1. Tilt your head back.

2. Place a finger on your cheek just under your eye and gently pull down until a "V" pocket is formed between your eyeball and your lower lid.

3. Place a small amount (about ½ inch) of TOBRADEX® (tobramycin and dexamethasone ophthalmic ointment). Do not let the tip of the tube touch your eye.

4. Look downward before closing your eye.

Not more than 8 g should be prescribed initially and the prescription should not be refilled without further evaluation as outlined in PRECAUTIONS above.

HOW SUPPLIED

HOW SUPPLIED: 3.5 g STERILE ointment supplied in an aluminum tube with a white polyethylene tip and white polyethylene cap (NDC 0078-0876-01)

STORAGE: Store at 2°C to 25°C (36°F to 77°F).

After opening, TOBRADEX (tobramycin and dexamethasone ophthalmic ointment) can be used until the expiration date on the tube.

Distributed by:
Novartis Pharmaceuticals Corporation
East Hanover, New Jersey 07936

© Novartis

T2021-62

May 2021

PRINCIPAL DISPLAY PANEL

NDC 0078-0876-01

TobraDex®

(tobramycin and dexamethasone ophthalmic ointment)

Sterile 3.5 g Net Wt.

Rx Only

NOVARTIS